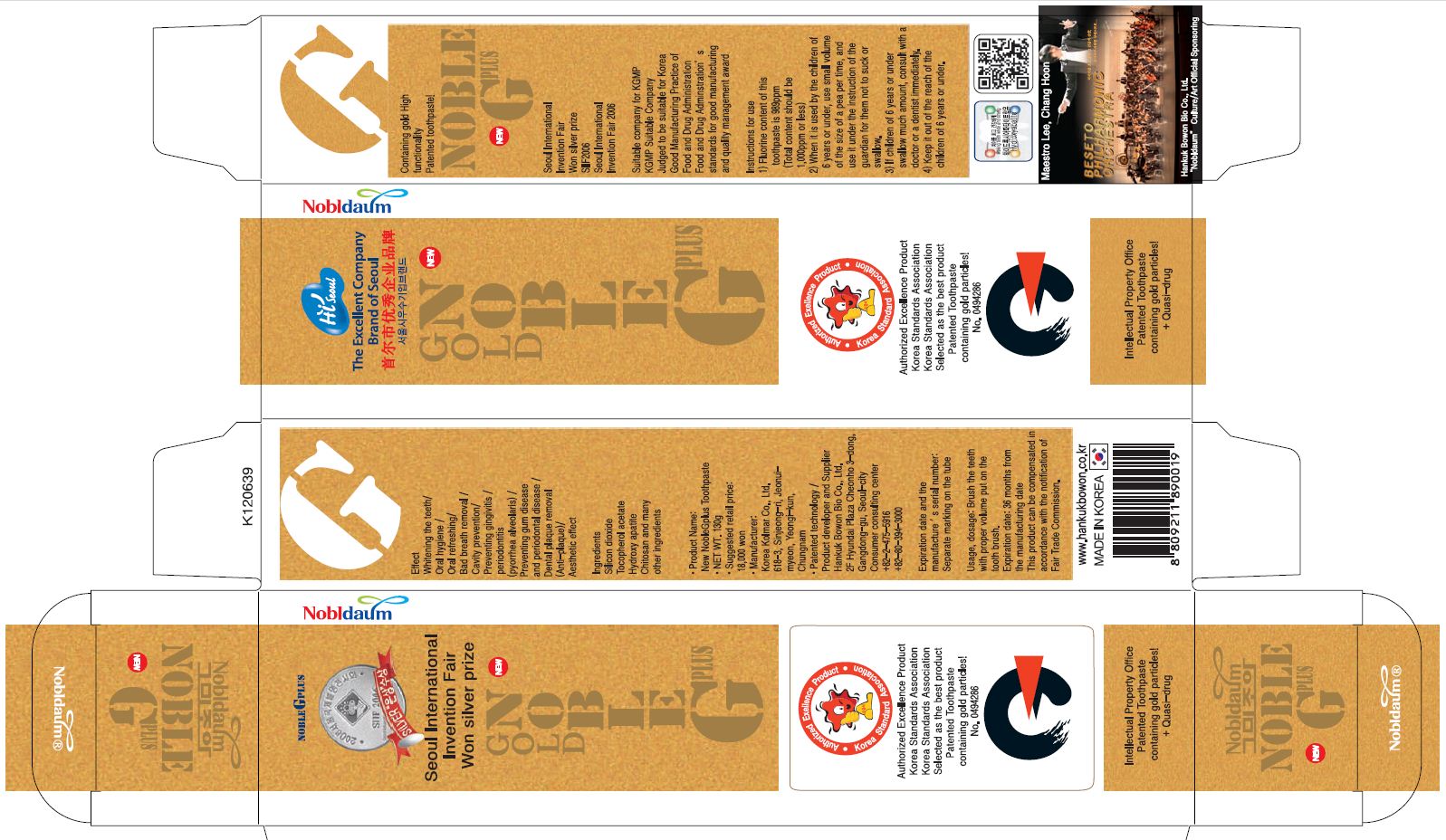 DRUG LABEL: Noble G Plus
NDC: 60319-3001 | Form: PASTE, DENTIFRICE
Manufacturer: Hankuk Bowonbio Co., Ltd
Category: otc | Type: HUMAN OTC DRUG LABEL
Date: 20191205

ACTIVE INGREDIENTS: XYLITOL 0.7 g/100 g
INACTIVE INGREDIENTS: WATER; SILICON DIOXIDE; SODIUM MONOFLUOROPHOSPHATE; HYDRATED SILICA; SORBITOL; CARBOXYMETHYLCELLULOSE SODIUM; SODIUM LAURYL SULFATE; SACCHARIN SODIUM ANHYDROUS; GOLD; GREEN TEA LEAF; POLYETHYLENE GLYCOL 1500; LEVOMENTHOL; TRIBASIC CALCIUM PHOSPHATE; CHITOSAN OLIGOSACCHARIDE; ISOSTEARIC ACID; POLYSORBATE 80

Drug Facts

active ingredient: xylitol

INACTIVE INGREDIENT

silicone dioxide, sodium monofluorophosphate, hydrated silicone dioxide, d-sorbitol, carboxymethylcellulose sodium, sodium lauryl sulfate, sodium saccharin, gold leaf, green tea extract, polyethylene glycol 1500, L-menthol, hydroxyapatite, chitosan, stearic acid, polysorbate 80, water

PURPOSE

whiten and strong teeth
removal of bad breath
prevention of gingivitis and periodontitis
prevention of periodontal diseases and gum diseases
removal of dental plaque

keep out of reach of the children

INDICATIONS AND USAGE

apply Proper Amount of the toothpaste on the tooth.

WARNINGS

■ For tooth only.
■ Avoid contact with eyes.
■ Do not swallow. If swallowed, get medical help.

DOSAGE AND ADMINISTRATION

brush your teeth by putting appropriate amount of tooth paste